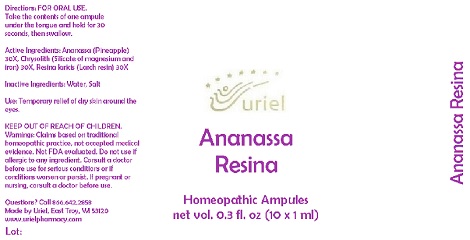 DRUG LABEL: Ananassa Resina
NDC: 48951-1330 | Form: LIQUID
Manufacturer: Uriel Pharmacy Inc.
Category: homeopathic | Type: HUMAN OTC DRUG LABEL
Date: 20191106

ACTIVE INGREDIENTS: PINEAPPLE 30 [hp_X]/1 mL; SILICON DIOXIDE 30 [hp_X]/1 mL; LARIX DECIDUA RESIN 30 [hp_X]/1 mL
INACTIVE INGREDIENTS: WATER; SODIUM CHLORIDE

Ananassa Resina

INDICATIONS AND USAGE

Directions: FOR ORAL USE.

DOSAGE AND ADMINISTRATION

Take the contents of one ampule under the tongue and hold for 30 seconds, then swallow.

ACTIVE INGREDIENT

Active Ingredients: Ananassa (Pineapple) 30X, Chrysolith (Silicate of magnesium and iron) 30X, Resina laricis (Larch resin) 30X

Inactive Ingredients: Water, Salt

PURPOSE

Use: Temporary relief of dry skin around the eyes.

KEEP OUT OF REACH OF CHILDREN.

WARNINGS

Warnings: Claims based on traditional homeopathic practice, not accepted medical evidence. Not FDA evaluated. Do not use if allergic to any ingredient. Consult a doctor before use for serious conditions or if conditions worsen or persist. If pregnant or nursing, consult a doctor before use.

Questions? Call 866.642.2858
Made by Uriel, East Troy, WI 53120
www.urielpharmacy.com